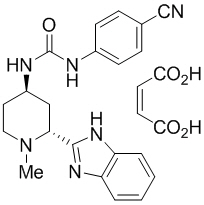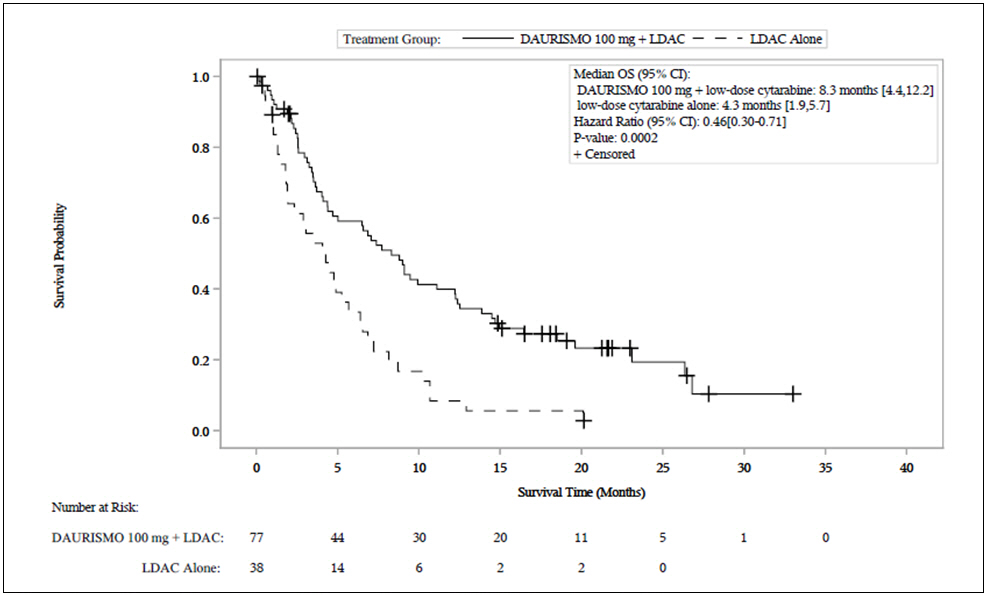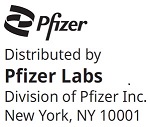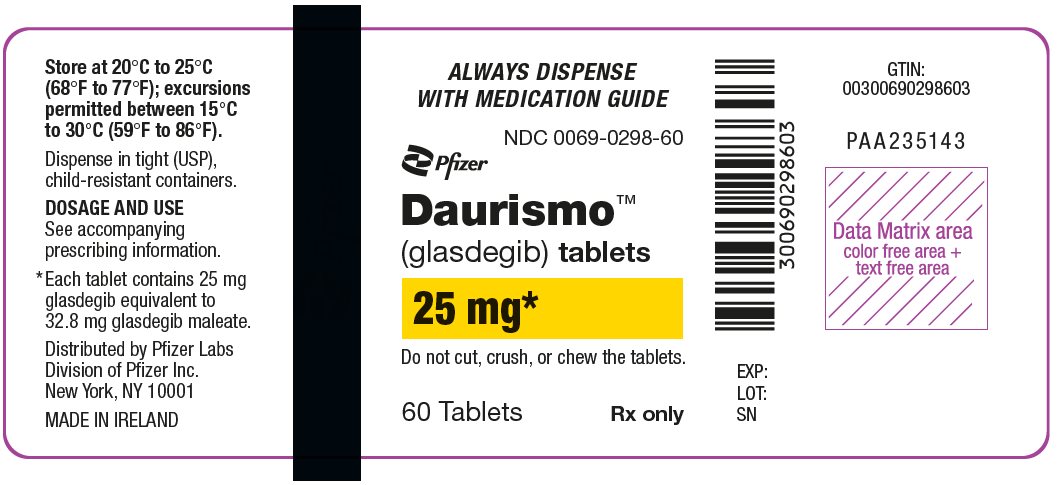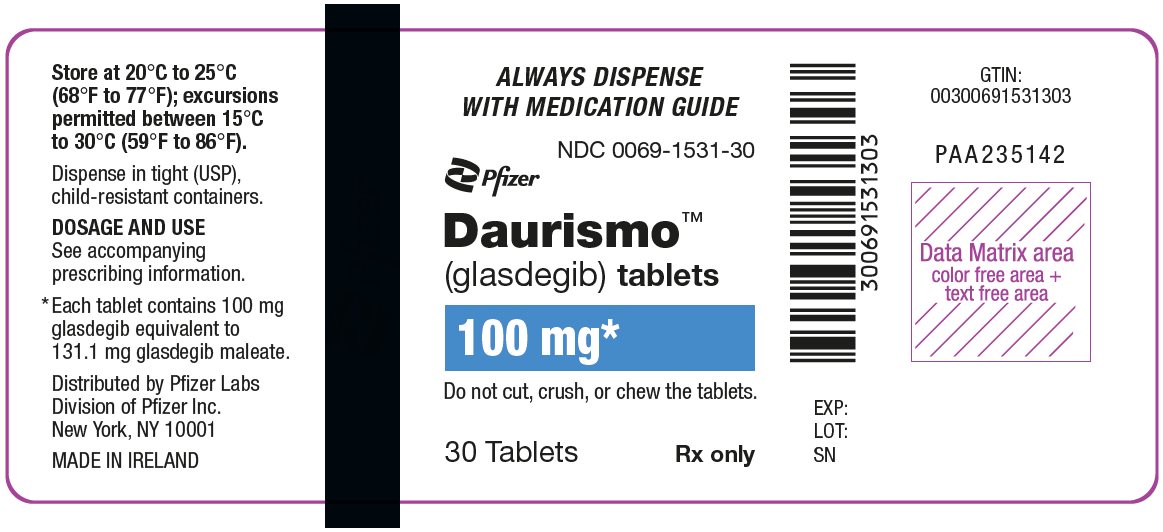 DRUG LABEL: Daurismo
NDC: 0069-0298 | Form: TABLET, FILM COATED
Manufacturer: Pfizer Laboratories Div Pfizer Inc
Category: prescription | Type: HUMAN PRESCRIPTION DRUG LABEL
Date: 20251212

ACTIVE INGREDIENTS: GLASDEGIB 25 mg/1 1
INACTIVE INGREDIENTS: MICROCRYSTALLINE CELLULOSE; ANHYDROUS DIBASIC CALCIUM PHOSPHATE; SODIUM STARCH GLYCOLATE TYPE A CORN; MAGNESIUM STEARATE; HYPROMELLOSE, UNSPECIFIED; TITANIUM DIOXIDE; LACTOSE MONOHYDRATE; POLYETHYLENE GLYCOL, UNSPECIFIED; TRIACETIN; FERRIC OXIDE YELLOW; FERRIC OXIDE RED

HIGHLIGHTS OF PRESCRIBING INFORMATION

These highlights do not include all the information needed to use DAURISMO safely and effectively. See full prescribing information for DAURISMO.
DAURISMO™ (glasdegib) tablets, for oral use
Initial U.S. Approval: 2018

WARNING: EMBRYO-FETAL TOXICITY

See full prescribing information for complete boxed warning.

- DAURISMO can cause embryo-fetal death or severe birth defects when administered to a pregnant woman. DAURISMO is embryotoxic, fetotoxic, and teratogenic in animals. (5.1, 8.1)
- Conduct pregnancy testing in females of reproductive potential prior to initiation of DAURISMO treatment. Advise females of reproductive potential to use effective contraception during treatment with DAURISMO and for at least 30 days after the last dose. (5.1, 8.1, 8.3)
- Advise males of the potential risk of exposure through semen and to use condoms with a pregnant partner or a female partner of reproductive potential during treatment with DAURISMO and for at least 30 days after the last dose to avoid potential drug exposure. (5.1, 8.3)

1 INDICATIONS AND USAGE

DAURISMO is a hedgehog pathway inhibitor indicated, in combination with low-dose cytarabine, for the treatment of newly-diagnosed acute myeloid leukemia (AML) in adult patients who are ≥75 years old or who have comorbidities that preclude use of intensive induction chemotherapy. (1)

2 DOSAGE AND ADMINISTRATION

Recommended dosage: 100 mg orally once daily. (2.1)

3 DOSAGE FORMS AND STRENGTHS

Tablets: 100 mg, 25 mg. (3)

4 CONTRAINDICATIONS

None. (4)

5 WARNINGS AND PRECAUTIONS

- Blood Donation: Advise patients not to donate blood or blood products during treatment with DAURISMO and for at least 30 days after the last dose. (5.1)
- QTc Interval Prolongation: Monitor electrocardiograms and electrolytes. If QTc prolongation occurs, interrupt treatment with DAURISMO. (2.2, 5.2)
- Musculoskeletal Adverse Reactions: Obtain creatine phosphokinase (CPK) and serum creatinine levels prior to initiating DAURISMO and as indicated clinically thereafter. Temporary dose interruption, dose reduction, or discontinuation of DAURISMO may be required for musculoskeletal adverse reactions or serum CPK elevation. (2.2, 5.3)

6 ADVERSE REACTIONS

Most common adverse reactions (incidence ≥20%) are anemia, fatigue, hemorrhage, febrile neutropenia, musculoskeletal pain, nausea, edema, thrombocytopenia, dyspnea, decreased appetite, dysgeusia, mucositis, constipation, and rash. (6.1)

To report SUSPECTED ADVERSE REACTIONS, contact Pfizer, Inc. at 1-800-438-1985 or FDA at 1-800-FDA-1088 or www.fda.gov/medwatch.

7 DRUG INTERACTIONS

- Strong CYP3A4 Inhibitors: Consider alternative therapies that are not strong CYP3A4 inhibitors or monitor for increased risk of adverse reactions, including QTc interval prolongation. (7)
- Strong CYP3A4 Inducers: Avoid concomitant use with DAURISMO. (7)
- Moderate CYP3A4 Inducers: Avoid concomitant use with DAURISMO. If, concomitant use cannot be avoided, increase the dose of DAURISMO. (2.3, 7)
- QTc Prolonging Drugs: Avoid co-administration with DAURISMO. If co-administration is unavoidable, monitor for increased risk of QTc interval prolongation. (7)

8 USE IN SPECIFIC POPULATIONS

Lactation: Advise women not to breastfeed. (8.2)

FULL PRESCRIBING INFORMATION

WARNING: EMBRYO-FETAL TOXICITY

DAURISMO can cause embryo-fetal death or severe birth defects when administered to a pregnant woman. DAURISMO is embryotoxic, fetotoxic, and teratogenic in animals [see Warnings and Precautions (5.1), Use in Specific Populations (8.1)].

Conduct pregnancy testing in females of reproductive potential prior to initiation of DAURISMO treatment. Advise females of reproductive potential to use effective contraception during treatment with DAURISMO and for at least 30 days after the last dose [see Warnings and Precautions (5.1), Use in Specific Populations (8.1, 8.3)].

Advise males of the potential risk of DAURISMO exposure through semen and to use condoms with a pregnant partner or a female partner of reproductive potential during treatment with DAURISMO and for at least 30 days after the last dose to avoid potential drug exposure [see Warnings and Precautions (5.1), Use in Specific Populations (8.3)].

1 INDICATIONS AND USAGE

DAURISMO is indicated, in combination with low-dose cytarabine, for the treatment of newly-diagnosed acute myeloid leukemia (AML) in adult patients who are ≥75 years old or who have comorbidities that preclude use of intensive induction chemotherapy.

2 DOSAGE AND ADMINISTRATION

2.1 Recommended Dosage and Schedule

The recommended dosage of DAURISMO is 100 mg orally once daily on days 1 to 28 in combination with cytarabine 20 mg subcutaneously twice daily on days 1 to 10 of each 28-day cycle in the absence of unacceptable toxicity or loss of disease control. For patients without unacceptable toxicity, treat for a minimum of 6 cycles to allow time for clinical response.

Administer DAURISMO with or without food. Do not split or crush DAURISMO tablets. Administer DAURISMO about the same time each day. If a dose of DAURISMO is vomited, do not administer a replacement dose; wait until the next scheduled dose is due. If a dose of DAURISMO is missed or not taken at the usual time, administer the dose as soon as possible and at least 12 hours prior to the next scheduled dose. Return to the normal schedule the following day. Do not administer 2 doses of DAURISMO within 12 hours.

2.2 Monitoring and Dosage Modifications

Assess complete blood counts, electrolytes, renal, and hepatic function prior to the initiation of DAURISMO and at least once weekly for the first month. Monitor electrolytes and renal function once monthly for the duration of therapy. Obtain creatine phosphokinase (CPK) levels prior to initiating DAURISMO and as indicated clinically thereafter (e.g., if muscle symptoms are reported). Monitor electrocardiograms (ECGs) prior to the initiation of DAURISMO, approximately one week after initiation, and then once monthly for the next two months to assess for QTc prolongation. Repeat ECG if abnormal. Certain patients may require more frequent and ongoing ECG monitoring [see Warnings and Precautions (5.2)]. Manage any abnormalities promptly [see Adverse Reactions (6.1)].

See Table 1 for dosage modification guidelines for patients who develop an adverse reaction.

Table 1. Recommended Dosage Modifications for Adverse Reactions
Adverse Reaction | Recommended Action
QTc interval prolongation on at least 2 separate electrocardiograms (ECGs) [see Warnings and Precautions (5.2)] | QTc interval greater than 480 ms to 500 ms | Assess electrolyte levels and supplement as clinically indicated. Review and adjust concomitant medications with known QTc interval-prolonging effects [see Drug Interactions (7)]. Monitor ECGs at least weekly for 2 weeks following resolution of QTc prolongation to less than or equal to 480 ms.
QTc interval prolongation on at least 2 separate electrocardiograms (ECGs) [see Warnings and Precautions (5.2)] | QTc interval greater than 500 ms | Assess electrolyte levels and supplement as clinically indicated. Review and adjust concomitant medications with known QTc interval-prolonging effects [see Drug Interactions (7)]. Interrupt DAURISMO. Resume DAURISMO at a reduced dosage of 50 mg once daily when QTc interval returns to within 30 ms of baseline or less than or equal to 480 ms. Monitor ECGs at least weekly for 2 weeks following resolution of QTc prolongation. Consider re-escalating the dosage of DAURISMO to 100 mg daily if an alternative etiology for the QTc prolongation can be identified.
QTc interval prolongation on at least 2 separate electrocardiograms (ECGs) [see Warnings and Precautions (5.2)] | QTc interval prolongation with life-threatening arrhythmia | Discontinue DAURISMO permanently.
Musculoskeletal adverse reactions [see Warnings and Precautions (5.3)] | Grade 3 [Grade 1 is mild, Grade 2 is moderate, Grade 3 is severe, Grade 4 is life-threatening.] or serum CPK elevation between 2.5 and 10 times upper limit of normal (ULN) | Obtain CPK and serum creatinine levels at least weekly until resolution of clinical signs and symptoms.; Interrupt DAURISMO until symptoms reduce to mild or return to baseline.; Resume DAURISMO at the same dose level, or at a reduced dose of 50 mg.; If toxicity recurs, discontinue DAURISMO.
Musculoskeletal adverse reactions [see Warnings and Precautions (5.3)] | Grade 4 or serum CPK elevation greater than 10 times ULN | Discontinue DAURISMO.
Hematologic toxicity [see Adverse Reactions (6.1)] | Platelets less than 10 Gi/L for more than 42 days in the absence of disease | Discontinue DAURISMO and low-dose cytarabine permanently.
Hematologic toxicity [see Adverse Reactions (6.1)] | Neutrophil count less than 0.5 Gi/L for more than 42 days in the absence of disease | Discontinue DAURISMO and low-dose cytarabine permanently.
Nonhematologic toxicity [see Adverse Reactions (6.1)] | Grade 3 | Interrupt DAURISMO and/or low-dose cytarabine until symptoms reduce to mild or return to baseline. Resume DAURISMO at the same dose level, or at a reduced dose of 50 mg. Resume low-dose cytarabine at the same dose level, or at a reduced dose of 15 mg or 10 mg. If toxicity recurs, discontinue DAURISMO and low-dose cytarabine. If toxicity is attributable to DAURISMO only, low-dose cytarabine may be continued.
Nonhematologic toxicity [see Adverse Reactions (6.1)] | Grade 4 | Discontinue DAURISMO and low-dose cytarabine permanently.
Abbreviations: CPK = creatine phosphokinase, ULN = upper limit of normal.

2.3 Dosage Modification for Concomitant Use with Moderate CYP3A4 Inducers

Avoid concomitant use of DAURISMO with moderate CYP3A4 inducers. If concomitant use of moderate CYP3A4 inducers cannot be avoided, increase the DAURISMO dosage as tolerated as shown in Table 2. After the moderate CYP3A4 inducer has been discontinued for 7 days, resume the DAURISMO dose taken prior to initiating the moderate CYP3A4 inducer [see Drug Interactions (7), Clinical Pharmacology (12.3)].

Table 2. Recommended Dosage of DAURISMO with Concomitant Use of Moderate CYP3A4 Inducers
Current Dosage | Adjusted Dosage
100 mg orally once daily | 200 mg orally once daily
50 mg orally once daily | 100 mg orally once daily

3 DOSAGE FORMS AND STRENGTHS

DAURISMO 100 mg tablets: round, pale orange film-coated tablet debossed with "Pfizer" on one side and "GLS 100" on the other.

DAURISMO 25 mg tablets: round, yellow film-coated tablet debossed with "Pfizer" on one side and "GLS 25" on the other.

4 CONTRAINDICATIONS

None.

5 WARNINGS AND PRECAUTIONS

5.1 Embryo-Fetal Toxicity

Based on its mechanism of action and findings from animal embryo-fetal developmental toxicity studies, DAURISMO can cause embryo-fetal death or severe birth defects when administered to a pregnant woman. There are no clinical data on the use of DAURISMO in pregnant women. In animal embryo-fetal developmental toxicity studies, glasdegib caused embryotoxicity, fetotoxicity and teratogenicity at maternal exposures that were less than the human exposure at the recommended human dose of 100 mg [see Use in Specific Populations (8.1, 8.2), Clinical Pharmacology (12.1)]. Advise pregnant women of the potential risk to the fetus.

Females of Reproductive Potential

DAURISMO is not recommended for use during pregnancy. Conduct pregnancy testing in female patients of reproductive potential prior to initiating DAURISMO treatment. Advise females of reproductive potential to use effective contraception during treatment with DAURISMO and for at least 30 days after the last dose. Advise women not to breastfeed during treatment with DAURISMO and for at least 30 days after the last dose [see Use in Specific Populations (8.2, 8.3)].

Males

Advise male patients with female partners of the potential risk of exposure through semen and to use effective contraception, including a condom, even after vasectomy, to avoid drug exposure to a pregnant partner or a female partner of reproductive potential during treatment with DAURISMO and for at least 30 days after the last dose [see Use in Specific Populations (8.3)].

Blood Donation

Advise patients not to donate blood or blood products while taking DAURISMO and for at least 30 days after the last dose of DAURISMO because their blood or blood products might be given to a female of reproductive potential.

5.2 QTc Interval Prolongation

Patients treated with DAURISMO can develop QTc prolongation and ventricular arrhythmias, including ventricular fibrillation and ventricular tachycardia. Of the 98 evaluable patients treated with DAURISMO 100 mg in combination with low-dose cytarabine in the clinical trial, 5% were found to have a QTc interval greater than 500 ms and 4% of patients had an increase from baseline QTc greater than 60 ms. The clinical trial excluded patients with baseline QTc of greater than 470 ms or with a history of long QT syndrome or uncontrolled cardiovascular disease.

Monitor electrocardiograms (ECGs) and electrolytes [see Dosage and Administration (2.2)]. Concomitant use of DAURISMO with drugs known to prolong the QTc interval and CYP3A4 inhibitors may increase the risk of QTc interval prolongation [see Drug Interactions (7), Clinical Pharmacology (12.2)]. In patients with congenital long QT syndrome, congestive heart failure, electrolyte abnormalities, or those who are taking medications known to prolong the QTc interval, more frequent ECG monitoring is recommended.

Interrupt DAURISMO if QTc increases to greater than 500 ms. Discontinue DAURISMO permanently for patients who develop QTc interval prolongation with signs or symptoms of life-threatening arrhythmia [see Dosage and Administration (2.2)].

5.3 Musculoskeletal Adverse Reactions

Musculoskeletal adverse reactions, which may be accompanied by CPK elevations, have occurred with DAURISMO and other drugs which inhibit the hedgehog (Hh) pathway. In BRIGHT AML 1003, musculoskeletal adverse reactions occurred in 45% of patients treated, with 2% (7/79) reported as Grade 3 or higher. The most frequent manifestations of musculoskeletal adverse reactions reported were musculoskeletal pain (30%) and muscle spasms (15%). Increased CPK laboratory values occurred in 16% of patients [see Adverse Reactions (6.1)].

Obtain baseline CPK levels prior to initiating DAURISMO and as clinically indicated (e.g., if muscle symptoms are reported). Obtain CPK and serum creatinine levels at least weekly in patients with musculoskeletal adverse reactions with concurrent CPK elevation greater than 2.5 times ULN until resolution of clinical signs and symptoms. Depending on the severity of symptoms, temporary dose interruption, dose reduction, or discontinuation of DAURISMO may be required for musculoskeletal adverse reactions or serum CPK elevation [see Dosage and Administration (2.2)].

6 ADVERSE REACTIONS

The following clinically-significant adverse reactions are described elsewhere in the labeling:

- QTc Interval Prolongation [see Warnings and Precautions (5.2)]
- Musculoskeletal Adverse Reactions [see Warnings and Precautions (5.3)]

6.1 Clinical Trials Experience

Because clinical trials are conducted under widely varying conditions, adverse reaction rates observed in the clinical trials of a drug cannot be directly compared to rates in the clinical trials of another drug and may not reflect the rates observed in practice.

The safety profile of DAURISMO is based on experience in the BRIGHT AML 1003 study for 111 adults with newly-diagnosed AML and 14 adults with other conditions for which DAURISMO is not indicated [see Clinical Studies (14)]. Patients were treated with DAURISMO 100 mg daily in combination with low-dose cytarabine (N=84) or low-dose cytarabine alone (N=41). The median duration of treatment in the DAURISMO with low-dose cytarabine arm was 83 days (range 3 to 972 days), and the median duration of treatment in the low-dose cytarabine alone arm was 47 days (range 6 to 239 days). The median exposure to DAURISMO in the DAURISMO with low-dose cytarabine arm was 76 days (range 3 to 954 days). Thirty-two patients (38%) were treated with DAURISMO with low-dose cytarabine for at least 6 months and 14 patients (17%) were treated for at least 1 year.

Serious adverse reactions were reported in 79% of patients treated in the DAURISMO with low-dose cytarabine arm. The most common (≥5%) serious adverse reactions in patients receiving DAURISMO with low-dose cytarabine were febrile neutropenia (29%), pneumonia (23%), hemorrhage (12%), anemia (7%), and sepsis (7%).

Dose reductions associated with adverse reactions were reported in 26% of patients treated with DAURISMO with low-dose cytarabine, and the most common reasons (≥2%) for dose reductions due to adverse reactions were muscle spasms (5%), fatigue (4%), febrile neutropenia (4%), anemia (2%), thrombocytopenia (2%), and ECG QT prolonged (2%). Adverse reactions leading to permanent discontinuation were reported in 36% of patients treated with DAURISMO with low-dose cytarabine, and the most common (≥2%) reasons for permanent discontinuation were pneumonia (6%), febrile neutropenia (4%), sepsis (4%), sudden death (2%), myocardial infarction (2%), nausea (2%), and renal insufficiency (2%).

Adverse reactions reported in the first 90 days of therapy on the BRIGHT AML 1003 study are shown in Table 3.

Table 3. Adverse Reactions Occurring in ≥10% of Patients [Adverse reactions with ≥10% incidence in the DAURISMO with low-dose cytarabine arm or the low-dose cytarabine arm are included.] [No Grade 5 events in the DAURISMO with low-dose cytarabine or low-dose cytarabine alone arm.] Within the First 90 Days of Therapy in BRIGHT AML 1003
Body System | Adverse Reactions | DAURISMO With Low-Dose Cytarabine N=84 |  | Low-Dose Cytarabine N=41
 |  | All Grades % | Grade ≥3 % | All Grades % | Grade ≥3 %
Blood and lymphatic system disorder | Anemia | 43 | 41 | 42 | 37
Blood and lymphatic system disorder | Hemorrhage [Hemorrhage includes petechiae, epistaxis, hematoma, contusion, rectal hemorrhage, anal hemorrhage, ecchymosis, gingival bleeding, hematuria, mouth hemorrhage, purpura, cerebral hemorrhage, eye contusion, eye hemorrhage, gastric hemorrhage, gastrointestinal hemorrhage, hematemesis, hemoptysis, hemorrhage, implant site hematoma, injection site bruising, retroperitoneal hematoma, thrombotic thrombocytopenic purpura, tracheal hemorrhage, conjunctival hemorrhage, disseminated intravascular coagulation, eyelid hematoma, hematochezia, hemorrhage intracranial, hemorrhoidal hemorrhage, lower gastrointestinal hemorrhage, retinal hemorrhage, and subdural hematoma.] | 36 | 6 | 42 | 12
Blood and lymphatic system disorder | Febrile neutropenia | 31 | 31 | 22 | 22
Blood and lymphatic system disorder | Thrombocytopenia | 30 | 30 | 27 | 24
General disorders and administration site conditions | Fatigue [Fatigue includes asthenia and fatigue.] | 36 | 14 | 32 | 7
General disorders and administration site conditions | Edema [Edema includes edema peripheral, edema, fluid overload, fluid retention, and swelling face.] | 30 | 0 | 20 | 2
General disorders and administration site conditions | Mucositis [Mucositis includes mucosal inflammation, oropharyngeal pain, stomatitis, anal ulcer, gingival pain, laryngeal inflammation, esophagitis, oral pain, aphthous ulcer, mouth ulceration, and pharyngeal inflammation.] | 21 | 1 | 12 | 0
General disorders and administration site conditions | Pyrexia | 18 | 1 | 22 | 2
General disorders and administration site conditions | Chest pain [Chest pain includes chest pain and non-cardiac chest pain.] | 12 | 1 | 2 | 0
Musculoskeletal and connective tissue disorders | Musculoskeletal pain [Musculoskeletal pain includes pain in extremity, arthralgia, back pain, myalgia, musculoskeletal pain, musculoskeletal chest pain, neck pain, and bone pain.] | 30 | 2 | 17 | 2
Musculoskeletal and connective tissue disorders | Muscle spasm [Muscle spasms includes muscle spasms and muscle tightness.] | 15 | 0 | 5 | 0
Gastrointestinal disorders | Nausea | 29 | 1 | 12 | 2
Gastrointestinal disorders | Constipation | 20 | 1 | 12 | 0
Gastrointestinal disorders | Abdominal pain [Abdominal pain includes abdominal pain, abdominal pain upper, and abdominal pain lower.] | 19 | 0 | 12 | 0
Gastrointestinal disorders | Diarrhea [Diarrhea includes diarrhea, colitis, and gastroenteritis.] | 18 | 4 | 22 | 0
Gastrointestinal disorders | Vomiting | 18 | 2 | 10 | 2
Respiratory thoracic and mediastinal disorders | Dyspnea [Dyspnea includes dyspnea, hypoxia, bronchospasm, and respiratory failure.] | 23 | 11 | 24 | 7
Respiratory thoracic and mediastinal disorders | Cough [Cough includes cough and productive cough.] | 18 | 0 | 15 | 2
Metabolism and nutrition disorders | Decrease appetite | 21 | 1 | 7 | 2
Nervous system disorders | Dysgeusia [Dysgeusia includes dysgeusia and ageusia.] | 21 | 0 | 2 | 0
Nervous system disorders | Dizziness | 18 | 1 | 7 | 0
Nervous system disorders | Headache | 12 | 0 | 10 | 2
Skin and subcutaneous tissue disorders | Rash [Rash includes rash, pruritus, erythema, skin ulcer, rash maculo-papular, and rash pruritic.] | 20 | 2 | 7 | 2
Infection and infestations | Pneumonia [Pneumonia includes pneumonia, pneumonia aspiration, and lung infection.] | 19 | 15 | 24 | 22
Investigations | Hyponatremia | 11 | 6 | 0 | 0
Investigations | Platelet count decreased | 15 | 15 | 10 | 10
Investigations | Weight decreased | 13 | 0 | 2 | 0
Investigations | White blood cell count decreased | 11 | 11 | 5 | 2
Cardiac disorders | Atrial arrhythmia [Atrial arrhythmia includes atrial fibrillation, bradycardia, tachycardia, and sinus tachycardia.] | 13 | 4 | 7 | 2
Renal and urinary disorders | Renal insufficiency [Renal insufficiency includes acute kidney injury, blood creatinine increased, oliguria, and renal failure.] | 19 | 5 | 10 | 0
Abbreviations: N = number of patients.
Preferred terms were retrieved by applying the Medical Dictionary for Regulatory Activities (MedDRA) version 19.1.
BRIGHT AML 1003 used National Cancer Institute Common Terminology Criteria for Adverse Events (CTCAE) version 4.0.
Adverse reactions include events that commenced within 28 days after the last treatment dose.

The adverse reactions muscle spasms (4 in 12 patients) and decreased appetite (2 in 10 patients) worsened (i.e. progressed from Grades ≤2 to Grade 3 or higher) after the first 90 days of therapy in BRIGHT AML 1003.

Additional clinically-significant adverse reactions occurring in <10% of patients treated with DAURISMO and low-dose cytarabine in BRIGHT AML 1003 include:

- Dental disorders: loose tooth and toothache
- Skin and subcutaneous tissue disorders: alopecia
- Cardiac disorders: QT interval prolonged

Changes in selected post-baseline laboratory values that were observed in patients with newly-diagnosed AML and other conditions for which DAURISMO is not indicated in the clinical trial are shown in Table 4.

Table 4. Selected Laboratory Abnormalities (≥15%) [Maximum severity based on the number of patients with available on-study laboratory data.] Within the First 90 Days of Therapy in BRIGHT AML 1003
 | DAURISMO with Low-Dose Cytarabine |  |  | Low-Dose Cytarabine
Laboratory Abnormality | N | All Grades % | Grade 3 or 4 [Grade 1 is mild, Grade 2 is moderate, Grade 3 is severe, Grade 4 is life-threatening.] % | N | All Grades % | Grade 3 or 4 %
Creatinine increased | 81 | 96 | 1 | 40 | 80 | 5
Hyponatremia | 81 | 54 | 7 | 39 | 41 | 8
Hypomagnesemia | 81 | 33 | 0 | 39 | 23 | 0
AST increased | 80 | 28 | 1 | 40 | 23 | 0
Blood bilirubin increased | 80 | 25 | 4 | 39 | 33 | 3
ALT increased | 80 | 24 | 0 | 40 | 28 | 3
Alkaline phosphatase increased | 80 | 23 | 0 | 40 | 28 | 3
Hyperkalemia | 81 | 16 | 1 | 40 | 8 | 3
CPK increased | 38 | 16 | 0 | 17 | 6 | 0
Hypokalemia | 81 | 15 | 0 | 40 | 23 | 0
Abbreviations: N = number of patients; AST = aspartate aminotransferase; ALT = alanine aminotransferase; CPK = creatinine phosphokinase.
BRIGHT AML 1003 used National Cancer Institute Common Terminology Criteria for Adverse Events (CTCAE) version 4.0.

The following laboratory abnormalities worsened (i.e. progressed from Grades ≤2 to Grade 3 or higher) after the first 90 days of therapy in BRIGHT AML 1003:

- hypophosphatemia (8 in 38 patients), creatinine increased (2 in 39 patients), and ALT increased (2 in 40 patients).

7 DRUG INTERACTIONS

Table 5. Drug Interactions with DAURISMO
Strong CYP3A Inhibitors
Clinical Impact | - Co-administration of DAURISMO with strong CYP3A inhibitors increased glasdegib plasma concentrations [see Clinical Pharmacology (12.3)]. - Increased glasdegib concentrations may increase the risk of adverse reactions including QTc interval prolongation [see Warnings and Precautions (5.2)].
Prevention or Management | - Consider alternative therapies that are not strong CYP3A4 inhibitors during treatment with DAURISMO. - Monitor patients for increased risk of adverse reactions including QTc interval prolongation [see Warnings and Precautions (5.2)].
Strong and Moderate CYP3A Inducers
Clinical Impact | Co-administration of DAURISMO with strong and moderate CYP3A inducers decreased glasdegib plasma concentrations [see Clinical Pharmacology (12.3)].; - Decreased glasdegib concentrations may reduce efficacy.
Prevention or Management | - Avoid co-administration of DAURISMO with strong and moderate CYP3A4 inducers. - If co-administration of DAURISMO with moderate CYP3A4 inducers cannot be avoided, increase the dose of DAURISMO [see Dosage and Administration (2.3)].
QTc Prolonging Drugs
Clinical Impact | Co-administration of DAURISMO with QTc prolonging drugs may increase the risk of QTc interval prolongation [see Warnings and Precautions (5.2)].
Prevention or Management | - Avoid co-administration of QTc prolonging drugs with DAURISMO or replace with alternative therapies. - If co-administration of a QTc prolonging drug is unavoidable, monitor patients for increased risk of QTc interval prolongation [see Warnings and Precautions (5.2)].

8 USE IN SPECIFIC POPULATIONS

8.1 Pregnancy

Risk Summary

Based on its mechanism of action and findings in animal embryo-fetal developmental toxicity studies, DAURISMO can cause fetal harm when administered to a pregnant woman [see Clinical Pharmacology (12.1)]. There are no clinical data on the use of DAURISMO in pregnant women to inform of a drug-associated risk of major birth defects and miscarriage. DAURISMO is not recommended for use during pregnancy. Conduct pregnancy testing in female patients of reproductive potential prior to initiating treatment with DAURISMO. Report pregnancy exposures to Pfizer at 1-800-438-1985.

In animal embryo-fetal developmental toxicity studies, repeat-dose oral administration of DAURISMO during organogenesis at maternal exposures that were less than the human exposure at the recommended dose resulted in embryotoxicity, fetotoxicity and teratogenicity in rats and rabbits (see Data). Advise pregnant women of the potential risk to a fetus.

The estimated background risk of major birth defects and miscarriage for the indicated population are unknown. Adverse outcomes in pregnancy occur regardless of the health of the mother or the use of medications. In the U.S. general population, the estimated background risk of major birth defects and miscarriage in clinically recognized pregnancies is 2% to 4% and 15% to 20%, respectively.

Data

Animal Data

In embryo-fetal developmental toxicity studies, glasdegib was orally administered to pregnant rats and rabbits at doses up to 100 mg/kg/day during the period of organogenesis. Glasdegib resulted in embryo-fetal lethality (e.g., increased postimplantation loss and decreased numbers of live fetuses) in rats and rabbits at 50 mg/kg/day and 5 mg/kg/day, respectively, at maternal exposures approximately 4-times and 3-times the human exposure at the recommended dose [based on Cmax (rat) and AUC (rabbit)]. Doses of ≥10 mg/kg in rat [approximately 0.6-times the human exposure (Cmax) at the recommended dose] and ≥5 mg/kg in rabbit resulted in fetal developmental abnormalities and malformations consisting of craniofacial malformations, malformed limbs, paws/digits, trunk and tail, dilation of brain, malpositioned/malformed eyes, misshapen head, small tongue, absent palate, teeth and viscera, diaphragmatic hernia, edema, heart defects, rib and vertebral abnormalities, malformed or absent structures in the appendicular skeleton.

8.2 Lactation

Risk Summary

There are no data on the presence of glasdegib or its active metabolites in human milk, the effects of the drug on the breastfed child, or its effect on milk production. Because of the potential for serious adverse reactions in a breastfed child from DAURISMO, advise women who are taking DAURISMO not to breastfeed or provide breast milk to infants or children during treatment with DAURISMO and for at least 30 days after the last dose.

8.3 Females and Males of Reproductive Potential

DAURISMO can cause fetal harm when administered to a pregnant woman [see Use in Specific Populations (8.1)].

Pregnancy Testing

Conduct pregnancy testing in females of reproductive potential within 7 days prior to initiating therapy with DAURISMO.

Contraception

Females

Advise females of reproductive potential to use effective contraception during treatment with DAURISMO and at least 30 days after the last dose.

Males

It is not known if glasdegib is present in semen. Advise males of the potential risk of exposure through semen and to use effective contraception, including a condom, even after a vasectomy, to avoid drug exposure to a pregnant partner or a female partner of reproductive potential during treatment with DAURISMO and for at least 30 days after the last dose. Advise males to not donate semen during treatment with DAURISMO for at least 30 days after the last dose [see Nonclinical Toxicology (13.1)].

Infertility

Males

Based on findings in repeat-dose animal toxicity studies in rats, DAURISMO may impair fertility in males of reproductive potential. Some effects on male reproductive organs did not recover [see Nonclinical Toxicology (13.1)]. Men should seek advice on effective fertility preservation before treatment.

8.4 Pediatric Use

The safety and effectiveness of DAURISMO have not been established in pediatric patients. In repeat-dose toxicity studies in rats, oral administration of DAURISMO resulted in adverse changes in growing bone, teeth, and testis. Effects on bone consisted of partial to complete closure of the epiphyseal plate. Effects in growing incisor teeth included degeneration/necrosis of ameloblasts, and complete tooth loss with oral ulceration. Reproductive tissue toxicity was evidenced by testicular degeneration and hypospermatogenesis. These effects in bone, teeth and testis were observed after administration of DAURISMO for 26 weeks at greater than or equal to 50 mg/kg/day corresponding to approximately 6.6-times the steady-state AUC in patients at the recommended human dose.

8.5 Geriatric Use

Of the total number of subjects in clinical studies of DAURISMO with low-dose cytarabine (N=88), 98% of the patients were age 65 years or older and 60% of the patients were age 75 years or older. There were insufficient patients younger than age 65 years to determine differences in adverse reactions reported from patients older than 65.

8.6 Renal Impairment

No dosage modification is recommended for patients with mild to severe renal impairment (estimated glomerular filtration rate [eGFR] 15 to 89 mL/min). Monitor patients with severe renal impairment (eGFR 15 to 29 mL/min) for increased risk of adverse reactions, including QTc interval prolongation, due to increased glasdegib concentrations [see Clinical Pharmacology (12.3)].

10 OVERDOSAGE

There is no specific antidote for DAURISMO. Management of DAURISMO overdose should include symptomatic treatment and ECG monitoring.

Glasdegib has been administered in clinical studies up to a dose of 640 mg/day. At the highest dosage, the adverse reactions that were dose limiting were nausea, vomiting, dehydration, hypotension, fatigue, and dizziness.

11 DESCRIPTION

DAURISMO (glasdegib) is a hedgehog pathway inhibitor. It is formulated with the maleate salt of glasdegib. The molecular formula for glasdegib maleate is C25H26N6O5. The molecular weight for glasdegib maleate is 490.51 Daltons. The chemical name of glasdegib maleate is 1-((2R,4R)-2-(1H-benzo[d]imidazol-2-yl)-1-methylpiperidin-4-yl)-3-(4-cyanophenyl) urea maleate. The molecular structure is shown below:

Glasdegib maleate is a white to pale colored powder with pKa values of 1.7 and 6.1. The aqueous solubility of glasdegib maleate is 1.7 mg/mL.

DAURISMO (glasdegib) is supplied as a film-coated tablet for oral use containing either 100 mg glasdegib (equivalent to 131.1 mg glasdegib maleate) or 25 mg of glasdegib (equivalent to 32.8 mg glasdegib maleate) together with microcrystalline cellulose, dibasic calcium phosphate anhydrous, sodium starch glycolate, and magnesium stearate as inactive ingredients in the tablet. The film-coating consists of Opadry II® Beige (33G170003) and Opadry II® Yellow (33G120011) containing: hypromellose, titanium dioxide, lactose monohydrate, macrogol, triacetin, iron oxide yellow, and iron oxide red.

12 CLINICAL PHARMACOLOGY

12.1 Mechanism of Action

Glasdegib is an inhibitor of the Hedgehog pathway. Glasdegib binds to and inhibits Smoothened, a transmembrane protein involved in hedgehog signal transduction.

In a murine xenotransplant model of human AML, glasdegib in combination with low-dose cytarabine, inhibited increases in tumor size and reduced the percentage of CD45+/CD33+ blasts in the marrow to a greater extent than glasdegib or low-dose cytarabine alone.

12.2 Pharmacodynamics

Cardiac Electrophysiology

The effect of glasdegib administration on corrected QT interval (QTc) was evaluated in a randomized, single-dose, double-blind, 4-way crossover, placebo- and open-label moxifloxacin-controlled study in 36 healthy subjects. At therapeutic plasma concentrations for the recommended dose, achieved with a single dose of 150 mg DAURISMO, the largest placebo and baseline-adjusted QTc interval change was 8 ms (90% CI: 6, 10 ms). At a two-fold therapeutic plasma concentration, achieved with a single dose of 300 mg DAURISMO, the QTc change was 13 ms (90% CI: 11, 16 ms). Glasdegib is associated with concentration-dependent QTc prolongation.

12.3 Pharmacokinetics

DAURISMO at 5 mg to 600 mg once daily (0.05 to 6 times the recommended dose) result in a dose proportional increase in glasdegib peak concentrations (Cmax) and area under the curve over the dosing interval (AUC0-Tau). Steady-state plasma levels are reached by 8 days of daily dosing. The median accumulation ratio of glasdegib ranged from 1.2 to 2.5 following once-daily dosing.

At DAURISMO 100 mg once daily, the geometric mean (geometric coefficient of variation, % CV) of glasdegib Cmax was 1252 ng/mL (44%) and AUC0-Tau was 17210 ng*hr/mL (54%) in patients with cancer.

Absorption

The mean absolute bioavailability of DAURISMO is 77%. Following 100 mg once daily dosing, glasdegib median time to peak concentrations (Tmax) at steady state ranged from 1.3 hours to 1.8 hours.

Effect of Food: A high-fat, high-calorie meal (total 800–1000 calories: 500–600 fat calories, 250 carbohydrate calories and 150 protein calories) reduced area under the curve over time to infinity (AUC0-INF) by 16% and Cmax by 31%.

Distribution

Glasdegib is 91% bound to human plasma proteins in vitro. The geometric mean (%CV) apparent volume of distribution (Vz/F) was 188 L (20%) in patients with hematologic malignancies.

Elimination

Glasdegib has a mean (± SD) half-life of 17.4 h (3.7) and geometric mean (%CV) apparent clearance of 6.45 L/h (25%) following 100 mg once daily dosing in patients with hematologic malignancies.

Metabolism

Glasdegib is primarily metabolized by the CYP3A4 pathway, with minor contributions by CYP2C8 and UGT1A9. Glasdegib accounts for 69% of the total circulating drug related material in plasma.

Excretion

Following a single oral dose of 100 mg radiolabeled glasdegib, 49% (17% unchanged) of the administered dose was eliminated in the urine and 42% (20% unchanged) of the administered dose was eliminated in the feces.

Specific Populations

Age (25 to 92 years), sex, race (White, Black, Asian), body weight (43.5 to 145.6 kg), mild hepatic impairment (total bilirubin ≤ ULN and AST > ULN or total bilirubin 1–1.5 × ULN and any AST), and mild renal impairment (creatinine clearance 60–89 mL/min) did not have clinically meaningful effects on the pharmacokinetics of glasdegib.

Patients with Renal Impairment

Following administration of a single dose of DAURISMO 100 mg, glasdegib AUC0-INF increased by 2.1-fold in subjects with moderate (eGFR 30 to 59 mL/min) and severe (eGFR 15 to 29 mL/min) renal impairment compared to subjects with normal renal function (eGFR ≥90 mL/min). The pharmacokinetics of glasdegib have not been studied in patients with end stage renal disease requiring hemodialysis.

Patients with Hepatic Impairment

Following administration of a single dose of DAURISMO 100 mg, glasdegib AUC0-INF increased by 11% in subjects with moderate hepatic impairment (Child-Pugh B) and decreased by 24% in subjects with severe hepatic impairment (Child-Pugh C) compared to subjects with normal hepatic function.

Drug Interaction Studies

Clinical Studies and Model-Informed Approaches

Effect of Strong CYP3A4 Inhibitors on Glasdegib: Co-administration of ketoconazole (a strong inhibitor of CYP3A4) with DAURISMO increased the glasdegib AUC0-INF by 2.4-fold and Cmax by 1.4-fold over glasdegib given alone [see Drug Interactions (7)].

Effect of Strong and Moderate CYP3A4 Inducers on Glasdegib: Co-administration of rifampin (a strong inducer of CYP3A4) with DAURISMO decreased glasdegib AUC0-INF by 70% and Cmax by 35% [see Drug Interactions (7)]. Co-administration of efavirenz (moderate CYP3A4 inducer) is predicted to decrease glasdegib AUC0-INF by 55% and Cmax by 25%.

Effect of Gastric Acid Reducing Agents on Glasdegib: Co-administration of rabeprazole (a proton pump inhibitor) with DAURISMO did not alter glasdegib AUC0-INF but decreased Cmax by 20%.

In Vitro Studies

Effect of Glasdegib on Cytochrome P450 (CYP) Substrates: Glasdegib does not inhibit CYP1A2, CYP2B6, CYP2C8, CYP2C9, CYP2C19, CYP2D6, or CYP3A, and does not induce CYP1A2, CYP2B6, and CYP3A in vitro.

Effect of Transporters on Glasdegib: Glasdegib is a substrate of P-glycoprotein (P-gp) and breast cancer resistance protein (BCRP).

Effect of Glasdegib on Transporters: Glasdegib inhibits P-gp, BCRP, multidrug and toxin extrusion (MATE) protein 1, and MATE-2K, but not organic anion transporting polypeptide (OATP)1B1, OATP1B3, organic anion transporter (OAT)1, OAT3, and organic cation transporter (OCT)2 in vitro.

13 NONCLINICAL TOXICOLOGY

13.1 Carcinogenesis, Mutagenesis, Impairment of Fertility

Carcinogenicity studies have not been performed with glasdegib.

Glasdegib was not mutagenic in vitro in the bacterial reverse mutation (Ames) assay and was not clastogenic in the in vitro chromosome aberration assay in human lymphocytes. Glasdegib was not clastogenic or aneugenic in the rat micronucleus assay.

Based on nonclinical safety findings, glasdegib has the potential to impair reproductive function in males. Men should seek advice on effective fertility preservation before treatment. In repeat-dose toxicity studies in rats, findings observed in the male reproductive tract included adverse testicular changes with glasdegib at doses ≥50 mg/kg/day, and consisted of minimal to severe hypospermatogenesis characterized by partial to complete loss of spermatogonia, spermatocytes and spermatids and testicular degeneration. Hypospermatogenesis did not recover whereas testicular degeneration did recover. The dose at which testicular effects were observed in male rats was identified as 50 mg/kg/day with corresponding systemic exposures that were approximately 6.6-times (based on AUC) those associated with the observed human exposure at the 100 mg once-daily dose.

14 CLINICAL STUDIES

The efficacy of DAURISMO in combination with low-dose cytarabine was evaluated in a multicenter, open-label, randomized study (Study BRIGHT AML 1003, NCT01546038) that included 115 patients age 55 years or older with newly-diagnosed AML who met at least one of the following criteria: a) age ≥75 years, b) severe cardiac disease, c) baseline Eastern Cooperative Oncology Group (ECOG) performance status of 2, or d) baseline serum creatinine >1.3 mg/dL. Patients were randomized 2:1 to receive DAURISMO at a 100 mg daily dose with low-dose cytarabine 20 mg subcutaneously twice daily on days 1 to 10 of a 28-day cycle (N=77) or low-dose cytarabine alone (N=38) in 28-day cycles until disease progression or unacceptable toxicity. Patients were stratified by cytogenetic risk (good/intermediate or poor).

The baseline demographic and disease characteristics are shown in Table 6. The two treatment arms were generally balanced with respect to the baseline demographics and disease characteristics (see Table 6).

Table 6. Baseline Demographic and Disease Characteristics in Patients with AML in BRIGHT AML 1003
Demographic and Disease Characteristics | DAURISMO With Low-Dose Cytarabine (N=77) | Low-Dose Cytarabine Alone (N=38)
Demographics
Age
Median (Min, Max) (Years) | 77 (64, 92) | 76 (58, 83)
≥75 years N (%) | 47 (61) | 23 (61)
Sex, N (%)
Male | 59 (77) | 23 (61)
Female | 18 (23) | 15 (39)
Race, N (%)
White | 75 (97) | 38 (100)
Black or African American | 1 (1) | 0 (0)
Asian | 1 (1) | 0 (0)
Disease History, N (%)
De Novo AML | 38 (49) | 18 (47)
Secondary AML | 39 (51) | 20 (53)
Prior Hypomethylating Agent Use | 11 (14) | 6 (16)
ECOG PS [Baseline ECOG PS was not reported for one patient in the DAURISMO with low-dose cytarabine arm.] , N (%)
0 to 1 | 35 (46) | 20 (53)
2 | 41 (53) | 18 (47)
Cytogenetic Risk Status, N (%)
Good/Intermediate | 48 (62) | 21 (55)
Poor | 29 (38) | 17 (45)
Baseline Severe Cardiac Disease | 51 (66) | 20 (53)
Baseline Serum Creatinine >1.3 mg/dL | 15 (19) | 5 (13)
Abbreviations: AML = acute myeloid leukemia; N = number of patients; ECOG PS = Eastern Cooperative Oncology Group Performance Status.

Efficacy was established on the basis of overall survival (OS) from the date of randomization to death from any cause. With a median follow-up of approximately 20 months, the DAURISMO with low-dose cytarabine arm was superior to low-dose cytarabine alone arm (Figure 1). The efficacy results are shown in Table 7. Improvement in OS was consistent across prespecified cytogenetic risk subgroups.

Table 7. Efficacy Results From BRIGHT AML 1003
Endpoint/Study Population | DAURISMO With Low-Dose Cytarabine | Low-Dose Cytarabine Alone
OS | N=77 | N=38
Median survival, months (95% CI) | 8.3 (4.4, 12.2) | 4.3 (1.9, 5.7)
Hazard ratio (95% CI) [Hazard ratio (DAURISMO with low-dose cytarabine/low-dose cytarabine alone) based on the Cox Proportional hazards model stratified by cytogenetic risk.] | 0.46 (0.30, 0.71)
p-value [1-sided p-value from log-rank test stratified by cytogenetic risk.] | 0.0002
CR | N=14 | N=1
CR rate (in %, 95% CI) | 18.2 (10.3, 28.6) | 2.6 (0.1, 13.8)
Abbreviations: AML = acute myeloid leukemia; N = number of patients; OS = overall survival; CI = confidence interval; CR = complete response.

Figure 1. BRIGHT AML 1003 – Kaplan-Meier Plot of Overall Survival for Patients with AML

Abbreviations: CI = confidence interval; OS = overall survival; LDAC = low-dose cytarabine.

16 HOW SUPPLIED/STORAGE AND HANDLING

DAURISMO is supplied in the following strengths and package configurations:

DAURISMO film-coated tablets
Package Configuration | Tablet Strength (mg) | NDC | Print (description)
30 count bottle | 100 mg | 0069-1531-30 | 100 mg strength: 11 mm round, pale orange film-coated tablet debossed with "Pfizer" on one side and "GLS 100" on the other
60 count bottle | 25 mg | 0069-0298-60 | 25 mg strength: 7 mm round, yellow film-coated tablet debossed with "Pfizer" on one side and "GLS 25" on the other

STORAGE AND HANDLING

Store at 20°C to 25°C (68°F to 77°F); excursions permitted between 15°C to 30°C (59°F to 86°F).

17 PATIENT COUNSELING INFORMATION

Advise the patient to read the FDA-approved patient labeling (Medication Guide).

Embryo-Fetal Toxicity

- Advise female patients of the potential risk to a fetus and to inform their healthcare provider of a known or suspected pregnancy. Advise female patients and female partners of male patients to contact their healthcare provider with a known or suspected pregnancy [see Warnings and Precautions (5.1), Use in Specific Populations (8.1, 8.3)].

Females and Males of Reproductive Potential

- Advise females of reproductive potential to use effective contraception during treatment with DAURISMO and for at least 30 days after the last dose.
- Advise males of the potential risk of exposure through semen and to use effective contraception, including a condom, even after a vasectomy, to avoid drug exposure to a pregnant partner or a female partner of reproductive potential during treatment with DAURISMO and for at least 30 days after the last dose [see Use in Specific Populations (8.3)].

Semen Donation

- Advise males not to donate semen during treatment with DAURISMO and for at least 30 days after the last dose of DAURISMO [see Use in Specific Populations (8.3)].

Lactation

- Advise women not to breastfeed during treatment with DAURISMO and for at least 30 days after the last dose of DAURISMO [see Use in Specific Populations (8.2)].

Blood Donation

- Advise patients not to donate blood or blood products during treatment with DAURISMO and for at least 30 days after the last dose of DAURISMO [see Warnings and Precautions (5.1)].

Infertility

- Advise males of reproductive potential of the potential for impaired fertility from DAURISMO. Advise male patients to seek advice on effective fertility preservation before treatment [see Use in Specific Populations (8.3), Nonclinical Toxicology (13.1)].

QTc Interval Prolongation

- Inform patients of signs and symptoms that may be indicative of significant QTc interval prolongation. Advise patients to contact their healthcare provider immediately in the event of syncope, pre-syncopal symptoms, and cardiac palpitations [see Warnings and Precautions (5.2)].

Musculoskeletal Adverse Reactions

- Advise patients starting therapy with DAURISMO of the risk of muscle-related adverse reactions.
- Advise patients to report promptly any new unexplained muscle pain, tenderness, or weakness occurring during treatment or that persists after discontinuing DAURISMO [see Warnings and Precautions (5.3)].

This product's label may have been updated. For current full prescribing information, please visit www.DAURISMO.com.

For medical information about DAURISMO, please visit www.pfizermedinfo.com or call 1-800-438-1985.

LAB-1284-4.0

MEDICATION GUIDE
DAURISMO™ (DOOR-is-moe)
(glasdegib) tablets

What is the most important information I should know about DAURISMO?
DAURISMO can cause your baby to die before it is born (be stillborn) or cause your baby to have severe birth defects.
For females who can become pregnant:

- You should talk to your healthcare provider about the risks of DAURISMO to your unborn child.
- Your healthcare provider will do a pregnancy test within 7 days before you start taking DAURISMO.
- You should not use DAURISMO during pregnancy.
- You should use effective birth control during treatment and for at least 30 days after your last dose of DAURISMO. Talk with your healthcare provider about what birth control method is right for you during this time.
- Talk to your healthcare provider right away if you have unprotected sex or if you think that your birth control has failed.
- Tell your healthcare provider right away if you become pregnant or think that you may be pregnant.

For males:

- It is not known if DAURISMO is present in semen. Do not donate semen during treatment with DAURISMO and for at least 30 days after your last dose.
- You should always use effective birth control, including a condom, even if you have had a vasectomy, during sex with female partners who are pregnant or who are able to become pregnant, during treatment with DAURISMO and for at least 30 days after your last dose to protect your female partner from being exposed to DAURISMO.
- Tell your healthcare provider right away if your partner becomes pregnant or thinks she is pregnant while you are taking DAURISMO.

Exposure to DAURISMO during pregnancy:
If you think that you or your female partner may have been exposed to DAURISMO during pregnancy, talk to your healthcare provider right away. If you become pregnant during treatment with DAURISMO, you or your healthcare provider should report your pregnancy to Pfizer at 1-800-438-1985.

What is DAURISMO?
DAURISMO is a prescription medicine that is used with the medicine cytarabine to treat newly-diagnosed acute myeloid leukemia (AML) in adults who:

- are 75 years of age or older, or
- have other medical conditions that prevent the use of standard chemotherapy.

It is not known if DAURISMO is safe and effective in children.

Before you take DAURISMO, tell your healthcare provider about all of your medical conditions, including if you:

- have heart problems, including a condition called long QT syndrome.
- abnormal blood salt (electrolytes) levels.
- have muscle pain or spasms.
- have kidney problems.
- are pregnant or plan to become pregnant. See "What is the most important information I should know about DAURISMO?"
- are breastfeeding or plan to breastfeed. It is not known if DAURISMO passes into your breast milk. Do not breastfeed or provide breast milk to infants or children during treatment with DAURISMO and for at least 30 days after the last dose. Talk to your healthcare provider about the best way to feed your baby during this time.

Tell your healthcare provider about the medicines you take, including prescription medicines, over-the-counter medicines, vitamins, and herbal supplements.

How should I take DAURISMO?

- Take DAURISMO with the medicine cytarabine exactly as your healthcare provider tells you.
- Take DAURISMO 1 time each day, at about the same time each day.
- Take DAURISMO with or without food.
- Do not chew, split or crush DAURISMO tablets.
- If you miss a dose of DAURISMO, take it as soon as you remember. If it is less than 12 hours before your next dose, just skip the missed dose and take your next dose at your regular time. Do not take 2 doses of DAURISMO within 12 hours.
- If you vomit after taking a dose of DAURISMO, do not take an extra dose, just take your next dose at your regular time.
- Your healthcare provider will perform certain tests to check you for side effects before and during treatment with DAURISMO.
- Your healthcare provider may change your dose, temporarily stop, or permanently stop treatment with DAURISMO if you have certain side effects. Do not change your dose or stop taking DAURISMO unless your healthcare provider tells you.
- If you take too much DAURISMO, call your healthcare provider or go to the nearest hospital emergency room right away.

What should I avoid while taking DAURISMO?

- Do not donate blood or blood products during treatment with DAURISMO and for at least 30 days after the last dose.
- Do not donate semen during treatment with DAURISMO and for at least 30 days after the last dose.

What are the possible side effects of DAURISMO?
DAURISMO can cause serious side effects, including:

- See "What is the most important information I should know about DAURISMO?"
- Changes in the electrical activity of your heart called QT prolongation. QT prolongation can cause irregular heartbeats that can be life-threatening. Tell your healthcare provider right away if you feel faint, lightheaded, dizzy, or feel your heart beating irregularly or fast during treatment with DAURISMO.
- Muscle Problems. Muscle problems are common with DAURISMO, but can also sometimes be serious. DAURISMO can increase your risk of muscle pain or muscle spasms. Tell your healthcare provider right away if you develop any new or worsening muscle spasms, pain, tenderness or weakness during and after treatment with DAURISMO. Your healthcare provider should do a blood test to check for muscle problems and to check your kidney function before you start taking DAURISMO, during treatment, and if you develop muscle problems.

The most common side effects of DAURISMO with cytarabine include:

- low red blood cell count (anemia)
- tiredness
- bleeding
- fever with low white blood cell count
- muscle pain
- swelling of arms or legs
- low platelet count

- nausea
- shortness of breath
- decreased appetite
- changes in taste
- pain or sores in your mouth or throat
- constipation
- rash

DAURISMO may affect fertility in males. Talk to your healthcare provider if this is a concern for you.
These are not all of the possible side effects of DAURISMO.
Call your doctor for medical advice about side effects. You may report side effects to FDA at 1-800-FDA-1088.

How should I store DAURISMO?

- Store DAURISMO at room temperature between 68°F to 77°F (20°C to 25°C).

Keep DAURISMO and all medicines out of the reach of children.

General information about the safe and effective use of DAURISMO.
Medicines are sometimes prescribed for purposes other than those listed in a Medication Guide. Do not use DAURISMO for a condition for which it was not prescribed. Do not give DAURISMO to other people, even if they have the same symptoms that you have. It may harm them. You can ask your healthcare provider or pharmacist for more information about DAURISMO that is written for health professionals.

What are the ingredients in DAURISMO?
Active ingredient: glasdegib
Inactive ingredients: microcrystalline cellulose, dibasic calcium phosphate anhydrous, sodium starch glycolate, and magnesium stearate.
Film-coating:
25 mg tablets: Opadry II Yellow (33G120011) containing hypromellose, titanium dioxide, lactose monohydrate, macrogol, triacetin, and iron oxide yellow.
100 mg tablets: Opadry II Beige (33G170003) containing hypromellose, titanium dioxide, lactose monohydrate, macrogol, triacetin, iron oxide yellow, and iron oxide red.

LAB-1285-4.0
For more information, go to www.DAURISMO.com or call 1-800-438-1985.

This Medication Guide has been approved by the U.S. Food and Drug Administration.

Revised: 12/2024

PRINCIPAL DISPLAY PANEL - 25 mg Tablet Bottle Label

ALWAYS DISPENSE
WITH MEDICATION GUIDE

NDC 0069-0298-60

Pfizer

Daurismo™
(glasdegib) tablets

25 mg*

Do not cut, crush, or chew the tablets.

60 Tablets
Rx only

PRINCIPAL DISPLAY PANEL - 100 mg Tablet Bottle Label

ALWAYS DISPENSE
WITH MEDICATION GUIDE

NDC 0069-1531-30

Pfizer

Daurismo™
(glasdegib) tablets

100 mg*

Do not cut, crush, or chew the tablets.

30 Tablets
Rx only